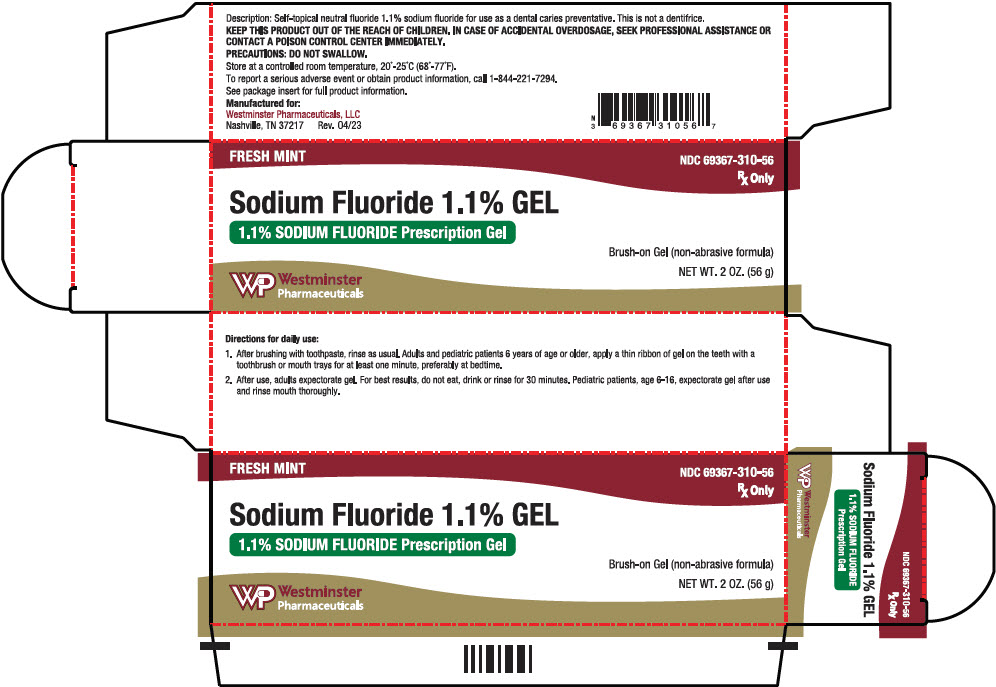 DRUG LABEL: Sodium Fluoride 1.1% Gel
NDC: 69367-310 | Form: GEL
Manufacturer: Westminster Pharmaceuticals, LLC
Category: prescription | Type: HUMAN PRESCRIPTION DRUG LABEL
Date: 20230705

ACTIVE INGREDIENTS: SODIUM FLUORIDE 5 mg/1 g
INACTIVE INGREDIENTS: WATER; SORBITOL; HYDROXYETHYL CELLULOSE (140 MPA.S AT 5%); SACCHARIN SODIUM; FD&C BLUE NO. 1; GLYCERIN; SODIUM BENZOATE; XYLITOL

SF 1.1% Gel 1.1% Sodium Fluoride - Brush-On Gel

DESCRIPTION

Self-topical neutral fluoride gel containing 1.1% (w/v) sodium fluoride for use as a dental caries preventive in pediatric patients and adults. This prescription product is not a dentifrice.

Active Ingredient: Sodium Fluoride, USP 1.1% (w/v).

Inactive Ingredients

FD&C Blue No. 1, glycerin, hydroxyethylcellulose, mint flavor, purified water, sodium benzoate, sodium saccharin, sorbitol, xylitol

CLINICAL PHARMACOLOGY

Frequent topical applications to the teeth with preparations having a relatively high fluoride content increase tooth resistance to acid dissolution and enhance penetration of the fluoride ion into tooth enamel.

INDICATIONS AND USAGE

A dental caries preventive, for once daily self-applied topical use. It is well established that 1.1% sodium fluoride is safe and extraordinarily effective as a caries preventive when applied frequently with mouthpiece applicators.^1-4 SF 1.1% Brush-On Gel in a squeeze-tube is easily applied onto a toothbrush as well as a mouthpiece tray. This prescription dental gel should be used once daily following use of a regular toothpaste unless otherwise instructed by your dental professional. May be used whether or not drinking water is fluoridated since topical fluoride cannot produce fluorosis. (See WARNINGS for exception.)

CONTRAINDICATIONS

Do not use in pediatric patients under age 6 years unless recommended by a dentist or physician.

WARNINGS

Prolonged daily ingestion may result in various degrees of dental fluorosis in pediatric patients under 6 years, especially if the water fluoridation exceeds 0.6 ppm, since younger pediatric patients frequently cannot perform the brushing process without significant swallowing. Use in pediatric patients under age 6 years requires special supervision to prevent repeated swallowing of gel which could cause dental fluorosis. Read directions carefully before using. If using a mouthpiece application, prolonged exposure (longer than 1 minute) may result in oral irritation, such as burning. KEEP THIS PRODUCT OUT OF THE REACH OF CHILDREN. IN CASE OF ACCIDENTAL OVERDOSAGE, SEEK PROFESSIONAL ASSISTANCE OR CONTACT A POISON CONTROL CENTER IMMEDIATELY.

PRECAUTIONS

Not for systemic treatment. DO NOT SWALLOW.

Carcinogenesis, Mutagenesis, Impairment of Fertility

In a study conducted in rodents, no carcinogenesis was found in male and female mice and female rats treated with fluoride at dose levels ranging from 4.1 to 9.1 mg/kg of body weight. Equivocal evidence of carcinogenesis was reported in male rats treated with 2.5 and 4.1 mg/kg of body weight. In a second study, no carcinogenesis was observed in rats, males or females, treated with fluoride up to 11.3 mg/kg of body weight. Epidemiological data provide no credible evidence for an association between fluoride, either naturally occurring or added to drinking water, and risk of human cancer.

Fluoride ion is not mutagenic in standard bacterial systems. It has been shown that fluoride ion has potential to induce chromosome aberrations in cultured human and rodent cells at doses much higher than those to which humans are exposed. In vivo data are conflicting. Some studies report chromosome damage in rodents, while other studies using similar protocols report negative results.

Potential adverse reproductive effects of fluoride exposure in humans has not been adequately evaluated. Adverse effects on reproduction were reported for rats, mice, fox, and cattle exposed to 100 ppm or greater concentrations of fluoride in their diet or drinking water. Other studies conducted in rats demonstrated that lower concentrations of fluoride (5 mg/kg of body weight) did not result in impaired fertility and reproductive capabilities.

Pregnancy

Pregnancy Category B

It has been shown that fluoride crosses the placenta of rats, but only 0.01% of the amount administered is incorporated in fetal tissue. Animal studies (rats, mice, rabbits) have shown that fluoride is not a teratogen. Maternal exposure to 12.2 mg fluoride/kg of body weight (rats) or 13.1 mg/kg of body weight (rabbits) did not affect the litter size or fetal weight and did not increase the frequency of skeletal or visceral malformations. Epidemiological studies conducted in areas with high levels of naturally fluoridated water showed no increase in birth defects. Heavy exposure to fluoride in utero development may result in skeletal fluorosis which becomes evident in childhood.

Nursing Mothers

It is not known if fluoride is excreted in human milk. However, many drugs are excreted in milk, and caution should be exercised when products containing fluoride are administered to a nursing woman. Reduced milk production was reported in farm-raised fox when animals were fed a diet containing a high concentration of fluoride (98-137 mg/kg of body weight). No adverse effects on parturition, lactation, or offspring were seen in rats administered fluoride up to 5 mg/kg of body weight.

Pediatric Use

The use of SF 1.1% Brush-On Gel in pediatric age groups 6 to 16 years as a caries preventive is supported by pioneering clinical studies with 1.1% sodium fluoride gels in mouth trays in students are 11-14 years conducted by Englander, et al.^2,3,4. Safety and effectiveness in pediatric patients below the age of 6 years have not been established. Please refer to the CONTRAINDICATIONS and WARNINGS sections.

ADVERSE REACTIONS

Allergic reactions and other idiosyncrasies have been rarely reported.

OVERDOSAGE

Accidental ingestion of large amounts of fluoride may result in acute burning in the mouth and sore tongue. Nausea, vomiting, and diarrhea may occur soon after ingestion (within 30 minutes) and are accompanies by salivation, hematemesis, and epigastric cramping and abdominal pain. These symptoms may persist for 24 hours. If less than 5 mg fluoride/kg body weight (i.e., less than 2.3 mg fluoride/lb body weight) have been ingested, give calcium (e.g., milk) orally to relieve gastrointestinal symptoms and observe for a few hours. If more than 5 mg fluoride/kg body weight (i.e., more than 2.3 mg fluoride/lb body weight) have been ingested, induce emesis, give orally soluble calcium (e.g., milk, 5% calcium gluconate or calcium lactate solution) and immediately seek medical assistance. For accidental ingestion of more than 15 mg fluoride/kg of body weight (i.e., more than 6.9 mg fluoride/lb body weight), induce vomiting and admit immediately to a hospital facility.

A treatment dose (a thin ribbon) of SF 1.1% Brush-On Gel contains 2 mg fluoride. A 2 oz. tube contains 266 mg fluoride.

DOSAGE AND ADMINISTRATION

Follow these instructions unless otherwise instructed by your dental professional: 1. After brushing thoroughly with toothpaste, rinse as usual. Adults and pedatric patients 6 years of age or older, apply a thin ribbon of gel to the teeth with a toothbrush or mouth trays once daily for at least one minute, preferably at bedtime. 2. After use, adults expectorate gel. For the best results, do not eat, drink, or rinse for 30 minutes. Pediatric patients, age 6-16, expectorate gel after use and rinse mouth thoroughly.

HOW SUPPLIED

2 oz. (56g) net wt. plastic tube.

Flavor: Fresh Mint

NDC 69367-310-56

STORAGE

Store at Controlled Room Temperature, 20° - 25° C (68° - 77° F).

Rx only

REFERENCES

1. American Dental Association, Council on Dental Therapeutics, Fluoride compounds, In: Accepted Dental Therapeutics, Ed. 40, Chicago, ADA, 405-407 (1984). 2. H.R. Englander et al., Clinical Anticaries Effect of Repeated Topical Sodium Fluoride Applications by Mouthpieces, JADA, 75, 638-644 (1967). 3. H.R. Englander et al., Residual Anticaries Effect of Repeated Topical Sodium Fluoride Applications by Mouthpieces, JADA, 78, 783-787 (1969). 4. H.R. Englander et al., Incremental Rates of Dental Caries After Repeated Topical Sodium Fluoride Applications in Children With Lifelong Consumption of Fluoridated Water, JADA, 82, 354-358, (1971).

You should call your doctor for medical advice about serious adverse events. To report a serious adverse event or obtain product information, contact Westminster Pharmaceuticals, LLC, 1-844-221-7294 or FDA at 1-800-FDA-1088 (Toll Free).

Manufactured for:
Westminster Pharmaceuticals, LLC
Nashville, TN 37217

Rev. 01/23

PRINCIPAL DISPLAY PANEL - 56 g Tube Carton

FRESH MINT

NDC 69367-310-56
Rx Only

Sodium Fluoride 1.1% GEL

1.1% SODIUM FLUORIDE Prescription Gel

Brush-on Gel (non-abrasive formula)
NET WT. 2 OZ. (56 g)

Westminster
Pharmaceuticals